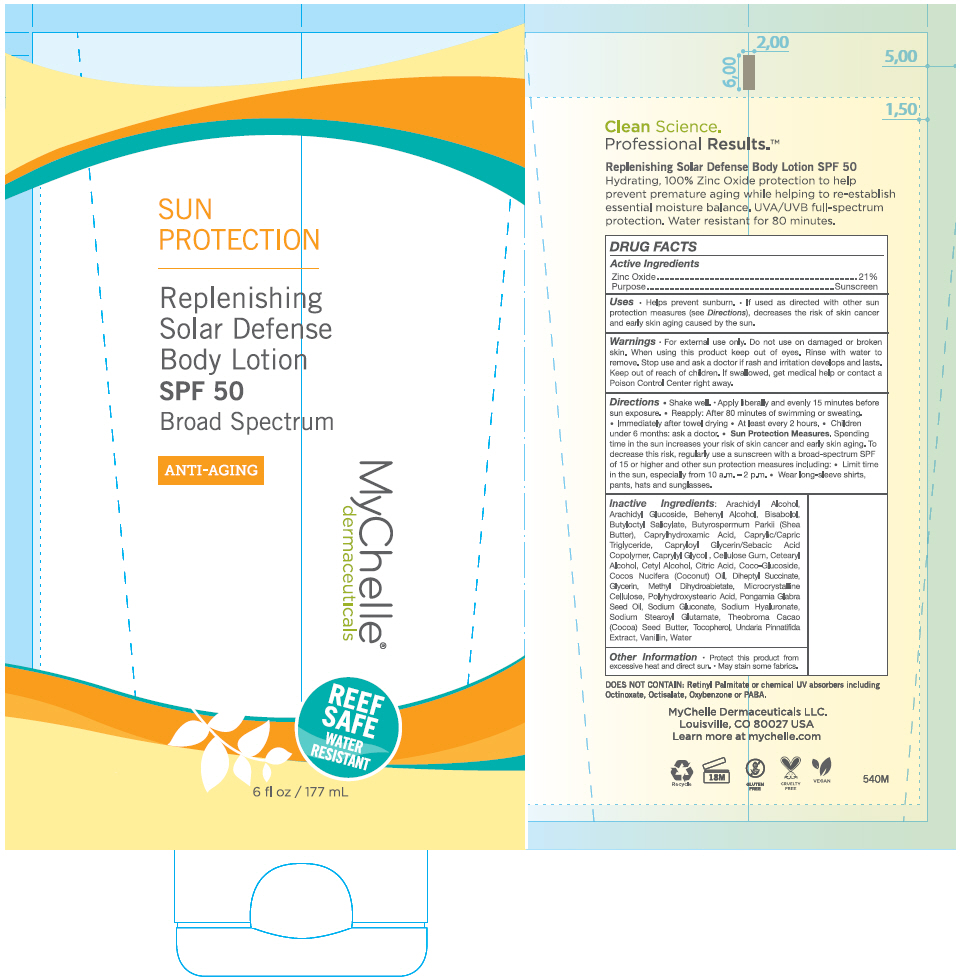 DRUG LABEL: MyChelle Dermaceuticals Replenishing Solar Defense Body 
NDC: 72805-020 | Form: LOTION
Manufacturer: French Transit, Ltd.
Category: otc | Type: HUMAN OTC DRUG LABEL
Date: 20190222

ACTIVE INGREDIENTS: Zinc Oxide 21 g/100 mL
INACTIVE INGREDIENTS: WATER; Microcrystalline Cellulose; CARBOXYMETHYLCELLULOSE SODIUM, UNSPECIFIED FORM; Caprylhydroxamic Acid; Caprylyl Glycol; Glycerin; HYALURONATE SODIUM; Sodium Gluconate; ANHYDROUS CITRIC ACID; Sodium Stearoyl Glutamate; COCONUT OIL; Diheptyl Succinate; CAPRYLOYL GLYCERIN/SEBACIC ACID COPOLYMER (2000 MPA.S); Methyl Dihydroabietate; SHEA BUTTER; COCOA BUTTER; KARUM SEED OIL; Butyloctyl Salicylate; LEVOMENOL; Tocopherol; POLYHYDROXYSTEARIC ACID (2300 MW); Cetyl Alcohol; CETOSTEARYL ALCOHOL; Coco Glucoside; Arachidyl Alcohol; DOCOSANOL; Arachidyl Glucoside; UNDARIA PINNATIFIDA; MEDIUM-CHAIN TRIGLYCERIDES; Vanillin

MyChelle® Dermaceuticals Replenishing Solar Defense Body Lotion
SPF 50 Broad Spectrum

DRUG FACTS

Active Ingredients

Zinc Oxide 21%

Purpose

Sunscreen

Uses

- Helps prevent sunburn.
- If used as directed with other sun protection measures (see Directions), decreases the risk of skin cancer and early skin aging caused by the sun.

Warnings

For external use only. Do not use on damaged or broken skin. When using this product keep out of eyes. Rinse with water to remove. Stop use and ask a doctor if rash and irritation develops and lasts.

Keep out of reach of children. If swallowed, get medical help or contact a Poison Control Center right away.

Directions

- Shake Well. Apply liberally and evenly 15 minutes before sun exposure.
- Reapply:
  - After 80 minutes of swimming or sweating.
  - Immediately after towel drying
  - At least every 2 hours
- Children under 6 months: ask a doctor.
- Sun Protection Measures. Spending time in the sun increases your risk of skin cancer and early skin aging. To decrease this risk, regularly use a sunscreen with a broad spectrum SPF of 15 or higher and other sun protection measures including:
  - Limit time in the sun, especially from 10 a.m. – 2 p.m.
  - Wear long-sleeve shirts, pants, hats and sunglasses.

Inactive Ingredients

Arachidyl Alcohol, Arachidyl Glucoside, Behenyl Alcohol, Bisabolol, Butyloctyl Salicylate, Butyrospermum Parkii (Shea Butter), Caprylhydroxamic Acid, Caprylic/Capric Triglyceride, Capryloyl Glycerin/Sebacic Acid Copolymer, Caprylyl Glycol, Cellulose Gum, Cetearyl Alcohol, Cetyl Alcohol, Citric Acid, Coco-Glucoside, Cocos Nucifera (Coconut) Oil, Diheptyl Succinate, Glycerin, Methyl Dihydroabietate, Microcrystalline Cellulose, Polyhydroxystearic Acid, Pongamia Glabra Seed Oil, Sodium Gluconate, Sodium Hyaluronate, Sodium Stearoyl Glutamate, Theobroma Cacao (Cocoa) Seed Butter, Tocopherol, Undaria Pinnatifida Extract, Vanillin, Water

Other information

Protect this product from excessive heat and direct sun. May stain some fabrics.

PRINCIPAL DISPLAY PANEL - 177 mL Tube Label

SUN
PROTECTION

Replenishing
Solar Defense
Body Lotion

SPF 50

Broad Spectrum

ANTI-AGING

MyChelle®
dermaceuticals

REEF
SAFE
WATER
RESISTANT

6 fl oz / 177 mL